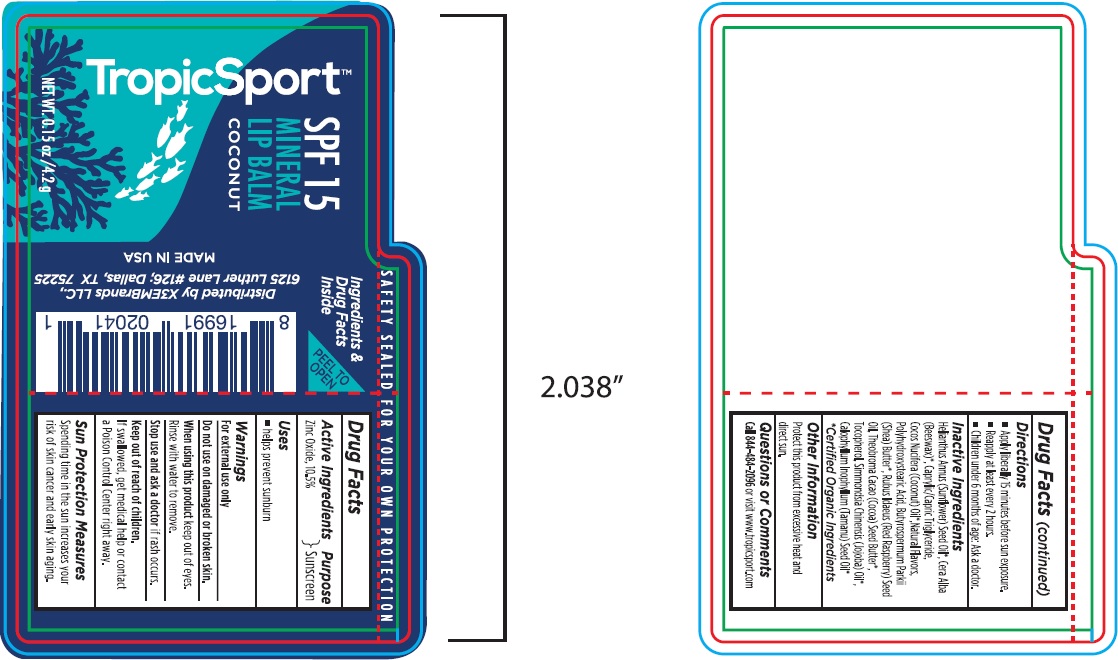 DRUG LABEL: LIP BALM
NDC: 62932-184 | Form: OINTMENT
Manufacturer: Private Label Select Ltd CO
Category: otc | Type: HUMAN OTC DRUG LABEL
Date: 20181123

ACTIVE INGREDIENTS: ZINC OXIDE 10 g/100 g
INACTIVE INGREDIENTS: COCONUT OIL; COCOA BUTTER; SIMMONDSIA CHINENSIS SEED WAX; SUNFLOWER OIL; RASPBERRY SEED OIL; TOCOPHEROL; TAMANU OIL; POLYHYDROXYSTEARIC ACID (2300 MW); SHEA BUTTER; HELIANTHUS ANNUUS SEED WAX; YELLOW WAX; CAPRYLIC/CAPRIC/LINOLEIC TRIGLYCERIDE

X3EM Tropicsport Mineral Lip Balm SPF15